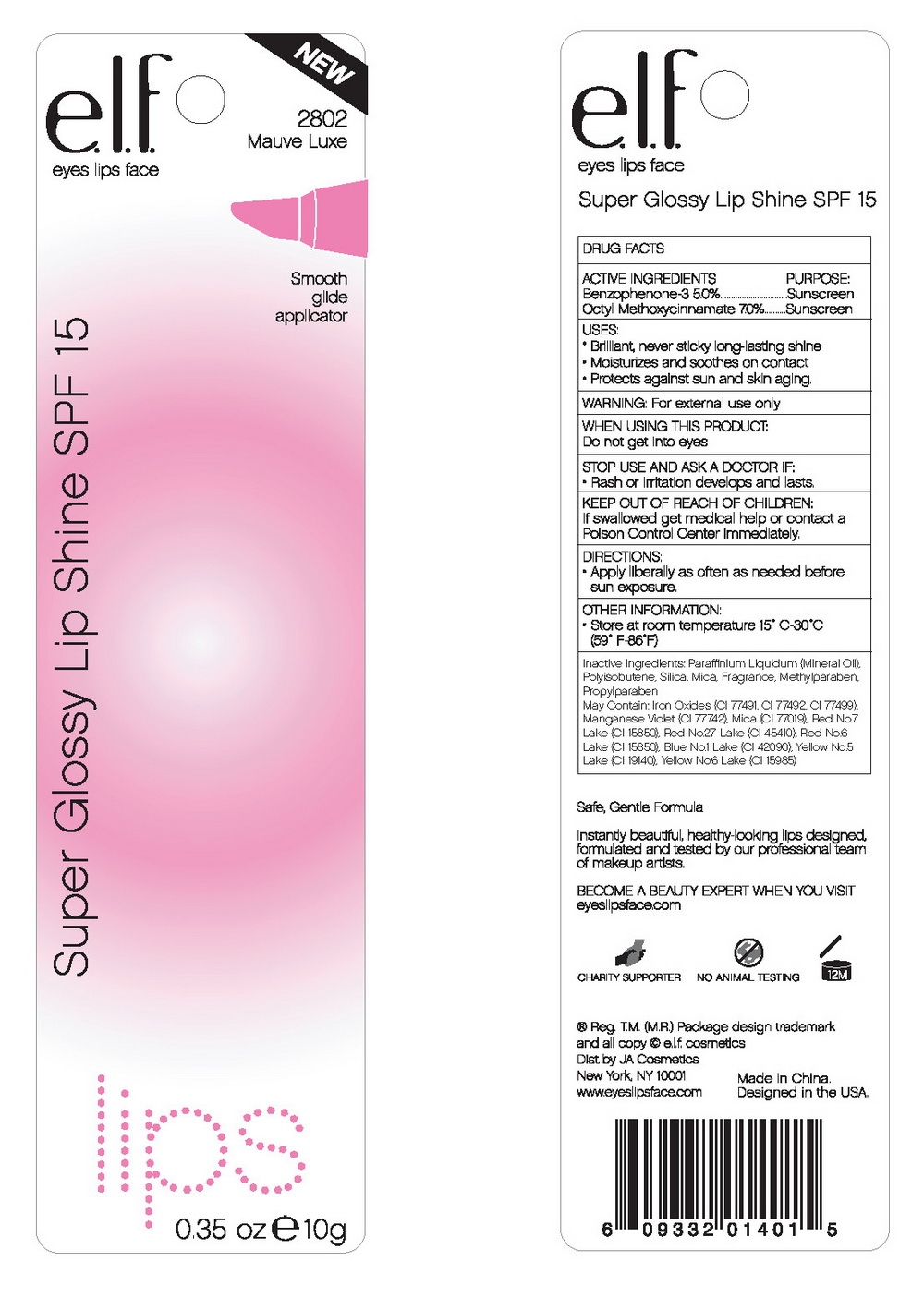 DRUG LABEL: ELF Super Glossy Lip Shine SPF 15
NDC: 52664-001 | Form: CREAM
Manufacturer: Hangzhou Facecare Cosmetics Co., Ltd.
Category: otc | Type: HUMAN OTC DRUG LABEL
Date: 20101115

ACTIVE INGREDIENTS: OXYBENZONE 5 g/100 g; OCTINOXATE 7 g/100 g
INACTIVE INGREDIENTS: POLYISOBUTYLENE (1200000 MW); SILICON DIOXIDE; MICA; METHYLPARABEN; PROPYLPARABEN; LIGHT MINERAL OIL; FERRIC OXIDE RED; FERRIC OXIDE YELLOW; FERROSOFERRIC OXIDE

Drug Fact

Active Ingredient:

Benzophenone-3: 5.0%

Octyl Methoxycinnamate: 7.0%

Purpose:

Sunscreen

Uses:

- Brilliant, never sticky long lasting shine
- Moisturizes and soothes on contact
- Protects sun and skin aging

Warning:

For external use only

When using this product:

Do not get into eyes

Stop Use and Ask a Doctor if:

Rash or irritation develops and lasts

Keep Out of Reach of Children:

If swallowed get medical help or contact a Poison Control Center immediately

Directions:

Apply liberally as often as needed before sun exposure.

STORAGE AND HANDLING

Other Imformation:

Store at room temperature 15-30C (59-86F)

Inactive Ingredient:

Paraffinium Liquidum (Mineral Oil), Polyisobutene, Silica, Mica, Fragrance, Methylparaben, Propylparaben.

May contain:

Iron Oxides (CI 77491, CI 77492, CI 77499), Manganese Violet (CI 77742), Mica (CI 77019), Red No. 7 Lake (CI 15850), Red No. 27 Lake (CI 45410), Red No. 6 Lake (CI 15851), Blue No. 1 Lake (CI 42090), Yellow No. 5 Lake (CI 19140), Yellow No. 6 Lake (CI 15985)

label